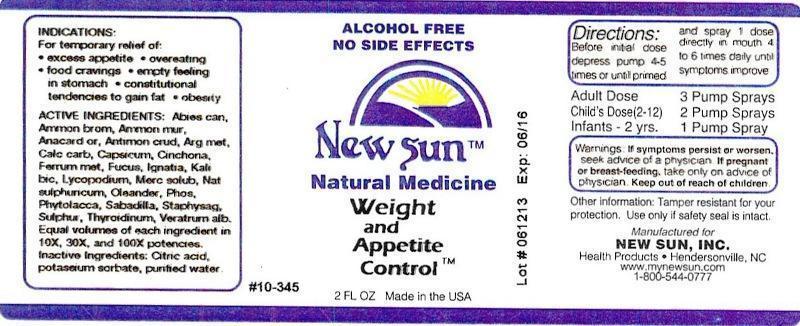 DRUG LABEL: Weight and Appetite Control
NDC: 66579-0070 | Form: LIQUID
Manufacturer: New Sun Inc.
Category: homeopathic | Type: HUMAN OTC DRUG LABEL
Date: 20141020

ACTIVE INGREDIENTS: TSUGA CANADENSIS BARK 10 [hp_X]/59 mL; TSUGA CANADENSIS FLOWER BUD 10 [hp_X]/59 mL; AMMONIUM BROMIDE 10 [hp_X]/59 mL; AMMONIUM CHLORIDE 10 [hp_X]/59 mL; SEMECARPUS ANACARDIUM JUICE 10 [hp_X]/59 mL; ANTIMONY TRISULFIDE 10 [hp_X]/59 mL; SILVER 10 [hp_X]/59 mL; OYSTER SHELL CALCIUM CARBONATE, CRUDE 10 [hp_X]/59 mL; CAPSICUM 10 [hp_X]/59 mL; CINCHONA OFFICINALIS BARK 10 [hp_X]/59 mL; IRON 10 [hp_X]/59 mL; FUCUS VESICULOSUS 10 [hp_X]/59 mL; STRYCHNOS IGNATII SEED 10 [hp_X]/59 mL; POTASSIUM DICHROMATE 10 [hp_X]/59 mL; LYCOPODIUM CLAVATUM SPORE 10 [hp_X]/59 mL; MERCURIUS SOLUBILIS 10 [hp_X]/59 mL; SODIUM SULFATE 10 [hp_X]/59 mL; NERIUM OLEANDER LEAF 10 [hp_X]/59 mL; PHOSPHORUS 10 [hp_X]/59 mL; PHYTOLACCA AMERICANA ROOT 10 [hp_X]/59 mL; SCHOENOCAULON OFFICINALE SEED 10 [hp_X]/59 mL; DELPHINIUM STAPHISAGRIA SEED 10 [hp_X]/59 mL; SULFUR 10 [hp_X]/59 mL; THYROID, UNSPECIFIED 10 [hp_X]/59 mL; VERATRUM ALBUM ROOT 10 [hp_X]/59 mL
INACTIVE INGREDIENTS: CITRIC ACID MONOHYDRATE; POTASSIUM SORBATE; WATER

Weight and Appetite Control

DOSAGE AND ADMINISTRATION

Directions: Before initial dose depress pump 4-5 times or until primed and spray 1 dose directly in mouth 4 to 6 times daily until symptoms improve.

Adult Dose: 3 Pump Sprays

Child's Dose (2-12): 2 Pump Sprays

Infants - 2 yrs: 1 Pump Spray

WARNINGS

Warnings: If symptoms persist or worsen, seek advice of a physician. If pregnant or breast-feeding, take only on advice of physician.

Keep out of reach of children.

Other information: Tamper resistant for your protection. Use only if safety seal is intact.

PURPOSE

Indications: For temporary relief of: •excess appetite •overeating •food cravings •empty feeling in stomach •constitutional tendencies to gain fat •obesity

ACTIVE INGREDIENT

Active Ingredients: Abies canadensis, Ammonium bromatum, Ammonium muriaticum, Anacardium orientale, Antimonium crudum, Argentum metallicum, Calcarea carbonica, Capsicum annuum, Cinchona officinalis, Ferrum metallicum, Fucus vesiculosus, Ignatia amara, Kali bichromicum, Lycopodium clavatum, Mercurius solubilis, Natrum sulphuricum, Oleander, Phosphorus, Phytolacca decandra, Sabailla, Staphysagria, Sulphur, Thyroidinum, Veratrum album. Equal volumes of each ingredient in 10X, 30X, 100X potencies.

Inactive Ingredient: Citric acid, potassium sorbate, purified water.

Indications: For temporary relief of:

- excess appetite
- overeating
- food cravings
- empty feeling in stomach
- constitutional tendencies to gain fat
- obesity